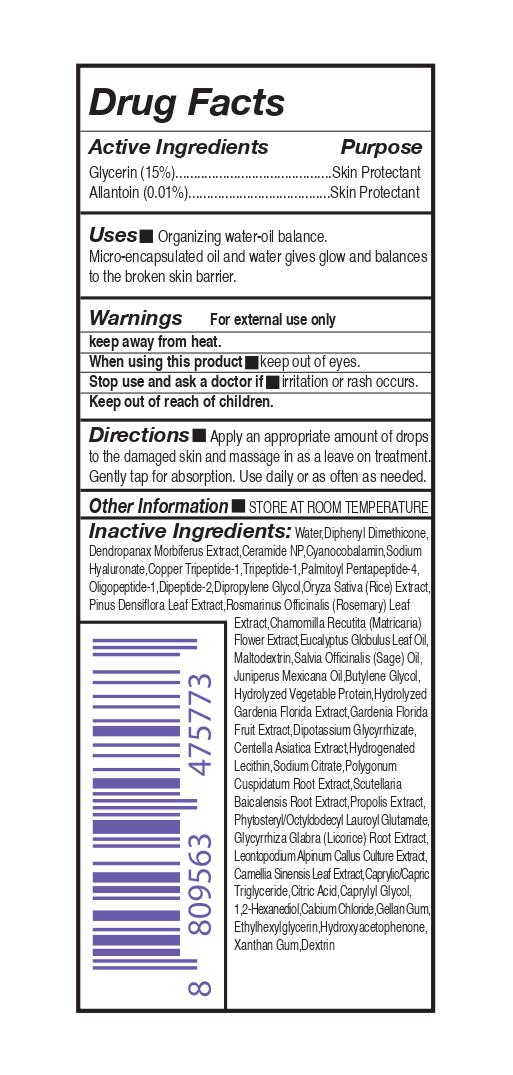 DRUG LABEL: repuera DermAtozyme 5% Hydro Essential Ampule
NDC: 81459-303 | Form: LIQUID
Manufacturer: ALLUV
Category: otc | Type: HUMAN OTC DRUG LABEL
Date: 20210128

ACTIVE INGREDIENTS: GLYCERIN 15 mg/100 mL; ALLANTOIN 0.01 mg/100 mL
INACTIVE INGREDIENTS: CYANOCOBALAMIN; HYDROLYZED SOY PROTEIN (ENZYMATIC; 2000 MW); HYDROGENATED SOYBEAN LECITHIN; LINALOOL, (+/-)-; DIPHENYL DIMETHICONE (100 CST); CHAMOMILE; BUTYLENE GLYCOL; GARDENIA JASMINOIDES FRUIT; POLYGONUM CUSPIDATUM ROOT; DEXTRIN PALMITATE (CORN; 20000 MW); JUNIPERUS DEPPEANA WOOD OIL; CENTELLA ASIATICA; SODIUM CITRATE; WATER; SCUTELLARIA BAICALENSIS ROOT; PREZATIDE COPPER; VALYLTRYPTOPHAN; DIPROPYLENE GLYCOL; PINUS DENSIFLORA LEAF; EUCALYPTUS OIL; MALTODEXTRIN; SAGE OIL; PROPOLIS WAX; PHYTOSTERYL/OCTYLDODECYL LAUROYL GLUTAMATE; GLYCYRRHIZA GLABRA; GREEN TEA LEAF; 1,2-HEXANEDIOL; CALCIUM CHLORIDE; ETHYLHEXYLGLYCERIN; HYDROXYACETOPHENONE; XANTHAN GUM; GERANIOL; LIMONENE, (+)-; CERAMIDE NP; HYALURONATE SODIUM; PREZATIDE; PALMITOYL PENTAPEPTIDE-4; RICE GERM; ROSEMARY; GLYCYRRHIZINATE DIPOTASSIUM; MEDIUM-CHAIN TRIGLYCERIDES; CITRIC ACID MONOHYDRATE; CAPRYLYL GLYCOL; GELLAN GUM (LOW ACYL)

81459-303 re'puera DermAtozyme 5% Hydro Essential Ampule

Active Ingridients

Glycerin (15%)

Allantoin (0.01%)

Purpose

skin protectant

Uses

Organizing water-oil balance.
Micro-encapsulated oil and water gives glow and balances
to the broken skin barrier.

Warnings

For external use only

keep away from heat.

When using this product

keep out of eyes.

Stop use and ask a doctor if

irritation or rash occurs.

Keep out of reach of children.

Directions

Apply an appropriate amount of drops
to the damaged skin and massage in as a leave on treatment.
Gently tap for absorption. Use daily or as often as needed.

Other Information

STORE AT ROOM TEMPERATURE

Inactive Ingredients

Water,Diphenyl Dimethicone, Dendropanax Morbiferus Extract,Ceramide NP,Cyanocobalamin,Sodium Hyaluronate,Copper Tripeptide-1, Tripeptide-1,Palmitoyl Pentapeptide-4, Oligopeptide-1, Dipeptide-2,Dipropylene Glycol,Oryza Sativa (Rice) Extract,Pinus Densiflora Leaf Extract,Rosmarinus Officinalis (Rosemary)Leaf Extract,Chamomilla Recutita (Matricaria) Flower Extract,Maltodextrin, Salvia Officinalis(Sage) Oil, Eucalyptus Globulus Leaf Oil, Juniperus Mexicana Oil,Butylene Glycol,Hydrolyzed Vegetable Protein,Hydrolyzed Gardenia Florida Extract,Gardenia Florida Fruit Extract,Dipotassium Glycyrrhizate, Centella Asiatica Extract,Hydrogenated Lecithin,Sodium Citrate,Polygonum Cuspidatum Root Extract,Scutellaria Baicalensis Root Extract,Propolis Extract, Phytosteryl/Octyldodecyl Lauroyl Glutamate,Glycyrrhiza Glabra(Licorice) Root Extract,Leontopodium Alpinum Callus Culture Extract,Camellia Sinensis Leaf Extract,Caprylic/Capric Triglyceride, Citric Acid,Caprylyl Glycol,1,2-Hexanediol, Calcium Chloride,Gellan Gum, Ethylhexylglycerin,Hydroxyacetophenone, Xanthan Gum,Dextrin